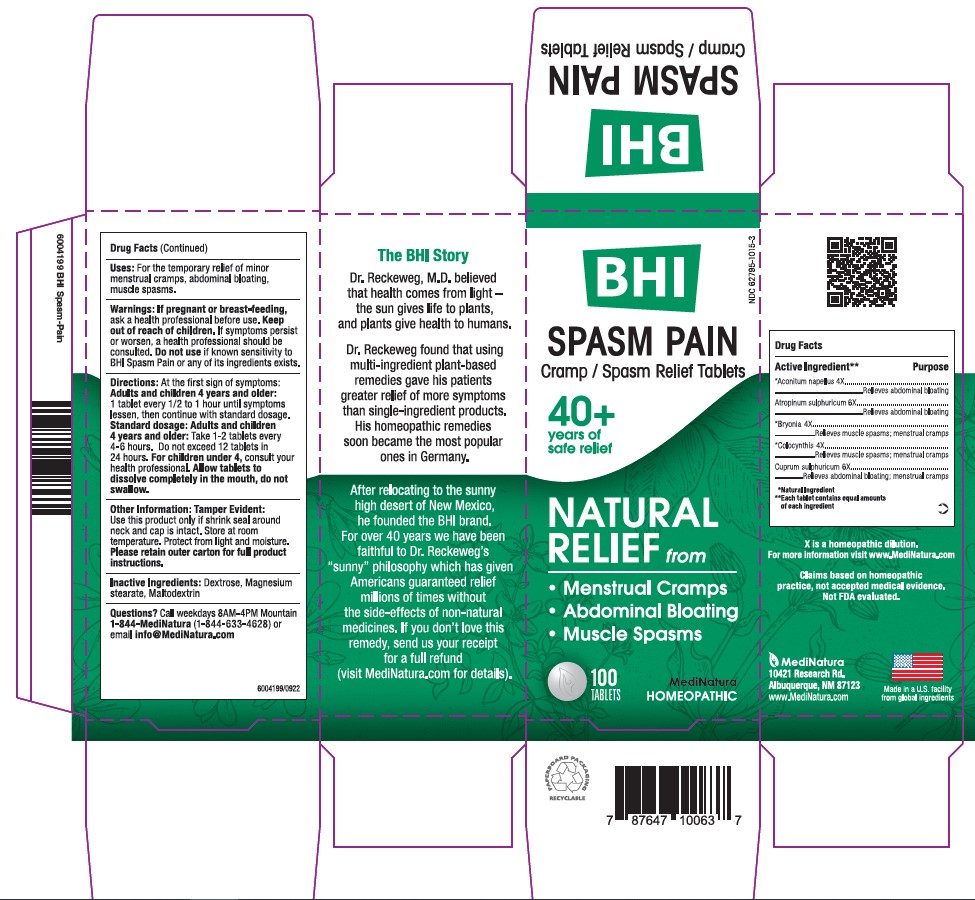 DRUG LABEL: BHI Spasm Pain
NDC: 62795-1015 | Form: TABLET
Manufacturer: MediNatura Inc
Category: homeopathic | Type: HUMAN OTC DRUG LABEL
Date: 20230928

ACTIVE INGREDIENTS: ATROPINE SULFATE 6 [hp_X]/1 1; ACONITUM NAPELLUS 4 [hp_X]/1 1; BRYONIA ALBA ROOT 4 [hp_X]/1 1; CITRULLUS COLOCYNTHIS FRUIT PULP 4 [hp_X]/1 1; CUPRIC SULFATE 6 [hp_X]/1 1
INACTIVE INGREDIENTS: MAGNESIUM STEARATE; MALTODEXTRIN; DEXTROSE

BHI Spasm Pain Tablet

ACTIVE INGREDIENTS

Each tablet contains: Atropinum sulphuricum 6X, *Aconitum napellus 4X, *Bryonia alba 4X, *Colocynthis 4X, Cuprum sulphuricum 6X 60 mg each.

*Natural Ingredients

INACTIVE INGREDIENT

Inactive Ingredients:Dextrose, Magnesium Stearate, Maltodextrin

PURPOSE

Cramp/Spasm Relief Tablets

Relieves:

• Menstrual Cramps

• Abdominal Bloating

• Muscle Spasms

DIRECTIONS

At first sign of symptoms: Adults and children 4 years and older: 1 tablet every 1/2 to 1 hour until symptoms lessen, then continue with standard dosage.

Standard dosage: Adults and children 4 years and older: Take 1-2 tablets every 4 to 6 hours. Do not exceed 12 tablets in 24 hours.

For children under 4, consult your health professional.

Allow tablets to dissolve completely in the mouth, do not swallow.

WARNINGS

If pregnant or breast-feeding, ask a health professional before use. Keep out of reach of children. If symptoms persist or worsen, a health professional should be consulted. Do not use if known sensitivity to Spasm Pain or any of its ingredients exists.

KEEP OUT OF REACH OF CHILDREN

PACKAGE LABEL

Add image transcription here...